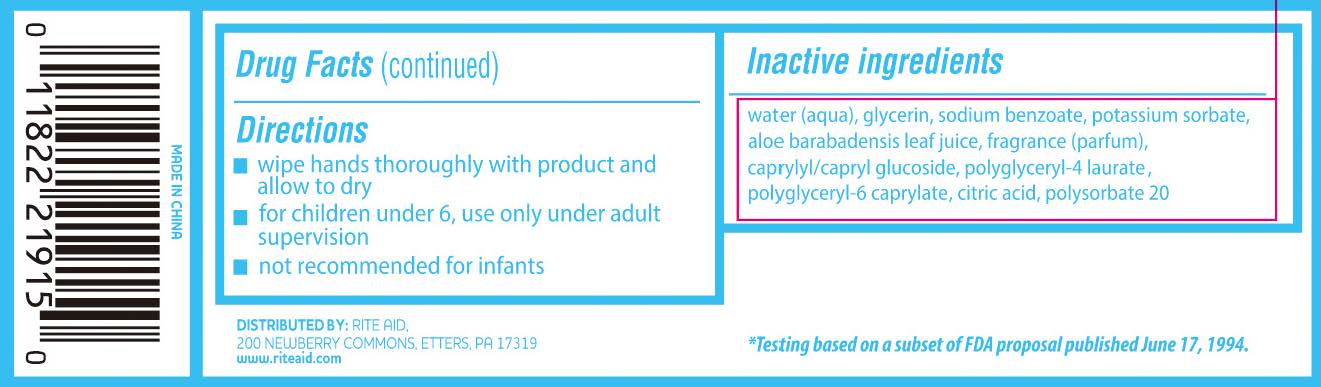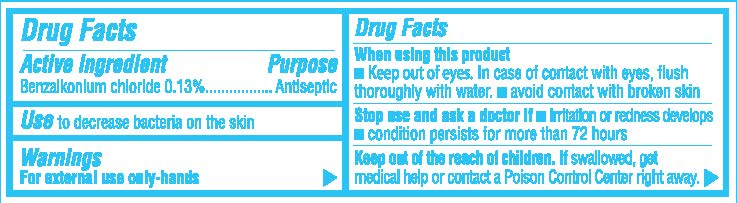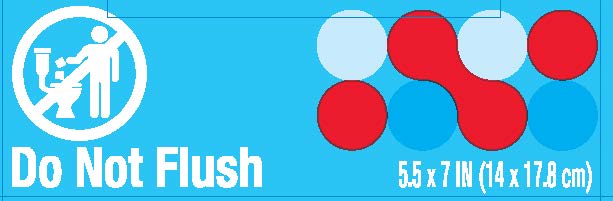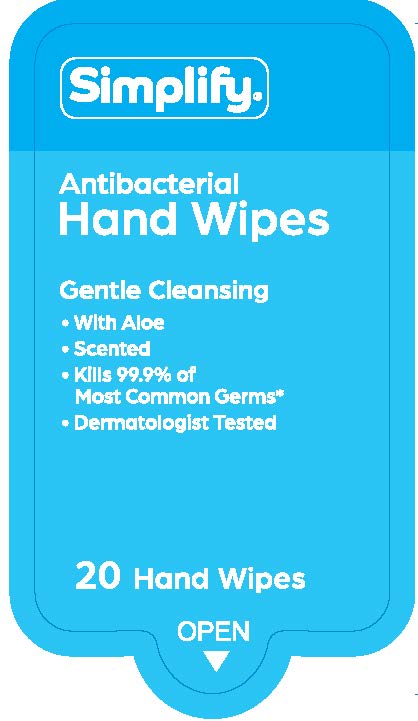 DRUG LABEL: Simplify Antibacterial Hand Wipes
NDC: 11822-0283 | Form: CLOTH
Manufacturer: Rite Aid Corporation
Category: otc | Type: HUMAN OTC DRUG LABEL
Date: 20251216

ACTIVE INGREDIENTS: BENZALKONIUM CHLORIDE 0.13 g/100 1
INACTIVE INGREDIENTS: POLYSORBATE 20; CAPRYLYL/CAPRYL OLIGOGLUCOSIDE; ANHYDROUS CITRIC ACID; WATER; ALOE VERA LEAF; GLYCERIN; POTASSIUM SORBATE; POLYGLYCERYL-6 CAPRYLATE; SODIUM BENZOATE; POLYGLYCERYL-4 LAURATE

Rite Aid - Wipe (20 count)

Drug Facts

Active Ingredient

Benzalkonium chloride 0.13%

Purpose

Antiseptic

Use

to decrease bacteria on the skin

Warnings

For external use only-hands

KEEP OUT OF REACH OF CHILDREN

Keep out of the reach of children. If swallowed, get

medical help or contact a Poison Control Center right away.

When using this product

- Keep out of eyes. In case of contact with eyes, flush

thoroughly with water.

- avoid contact with broken skin

Stop use and ask a doctor if

- irritation or redness develops
- condition persists for more than 72 hours

Drug Facts (continued)

Directions

- wipe hands thoroughly with product and

allow to dry

- for children under 6, use only under adult

supervision

- not recommended for infants

Inactive Ingredients

water (aqua), glycerin, sodium benzoate, potassium sorbate,
aloe barabadensis leaf juice, fragrance (parfum),
caprylyl/capryl glucoside, polyglyceryl-4 laurate/sebacate,
polyglyceryl-6 caprylate/caprate, citric acid, polysorbate 20

PACKAGE LABEL

Simplify®

Antibacterial

Hand Wipes

Gentle Cleansing

- With aloe
- Scented
- Kills 99.9% of

Most Common Germs*

- Dermatologist Tested

20 Hand Wipes

OPEN

Do Not Flush

5.5 x 7 in (14 x 17.8 cm)

DISTRIBUTED BY: RITE AID,
2.00 NEWBERRY COMMONS, ETTERS. PA 17319
www.riteaid.com

*Testing based on a subset of FDA proposal published June 17, 1994.